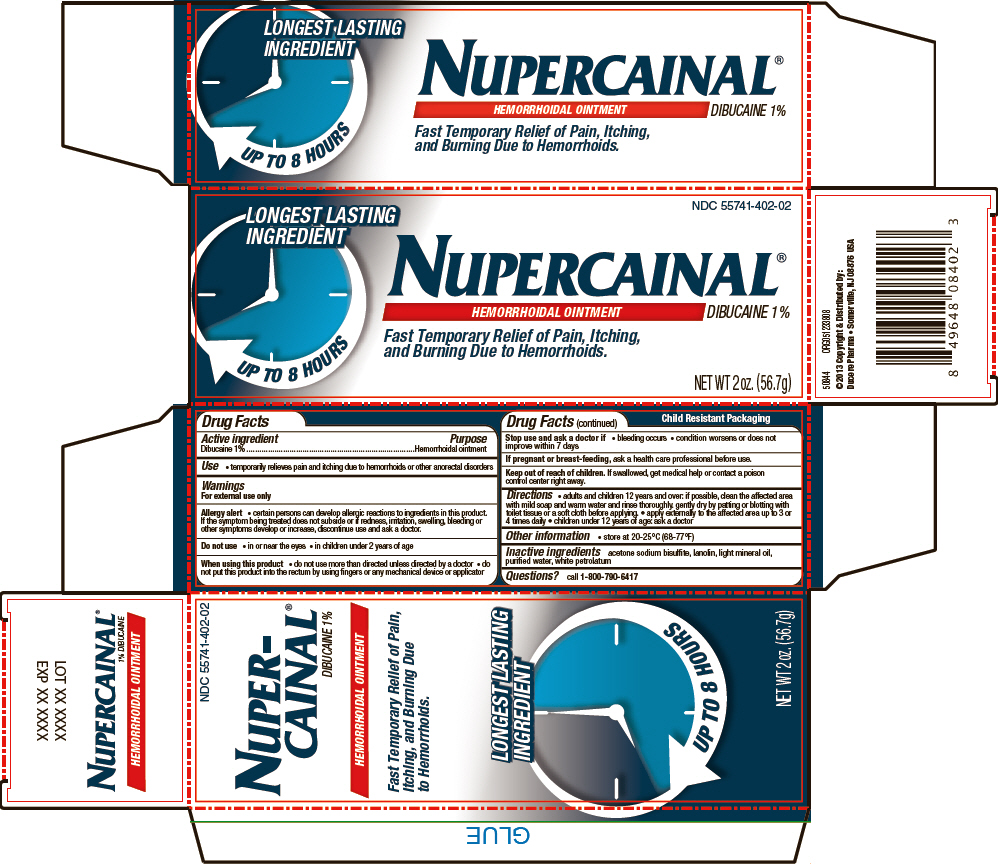 DRUG LABEL: Nupercainal
NDC: 55741-402 | Form: OINTMENT
Manufacturer: Dr. Reddy's Laboratories Inc.
Category: otc | Type: HUMAN OTC DRUG LABEL
Date: 20160615

ACTIVE INGREDIENTS: Dibucaine 1 g/100 g
INACTIVE INGREDIENTS: acetone sodium bisulfite; lanolin; light mineral oil; water; petrolatum

Nupercainal®

Drug Facts

Active ingredient

Dibucaine 1%

Purpose

Hemorrhoidal ointment

Use

- temporarily relieves pain and itching due to hemorrhoids or other anorectal disorders

Warnings

For external use only

Allergy alert

- certain persons can develop allergic reactions to ingredients in this product. If the symptom being treated does not subside or if redness, irritation, swelling, bleeding or other symptoms develop or increase, discontinue use and ask a doctor.

Do not use

- in or near the eyes
- in children under 2 years of age

When using this product

- do not use more than directed unless directed by a doctor
- do not put this product into the rectum by using fingers or any mechanical device or applicator

Stop use and ask a doctor if

- bleeding occurs
- condition worsens or does not improve within 7 days

PREGNANCY OR BREAST FEEDING

If pregnant or breast-feeding, ask a health care professional before use.

Keep out of reach of children. If swallowed, get medical help or contact a poison control center right away.

Directions

- adults and children 12 years and over: if possible, clean the affected area with mild soap and warm water and rinse thoroughly. gently dry by patting or blotting with toilet tissue or a soft cloth before applying.
- apply externally to the affected area up to 3 or 4 times daily
- children under 12 years of age: ask a doctor

Other information

- store at 20-25°C (68-77°F)

Inactive ingredients

acetone sodium bisulfite, lanolin, light mineral oil, purified water, white petrolatum

Questions?

call 1-800-790-6417

PRINCIPAL DISPLAY PANEL - 56.7g Tube Box

LONGEST LASTING
INGREDIENT

UP TO 8 HOURS

NDC 55741-402-02

NUPERCAINAL®
HEMORRHOIDAL OINTMENT
DIBUCAINE 1%

Fast Temporary Relief of Pain, Itching,
and Burning Due to Hemorrhoids.

NET WT 2 oz. (56.7g)